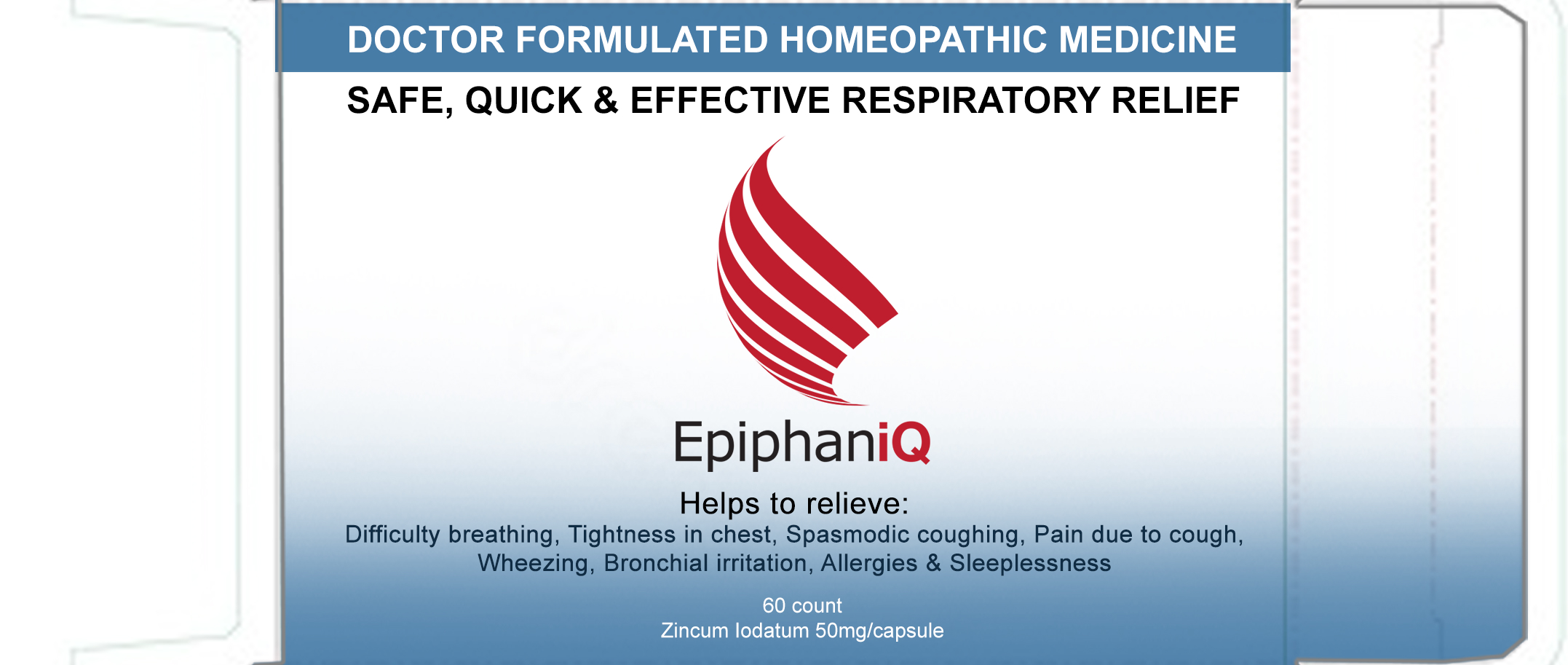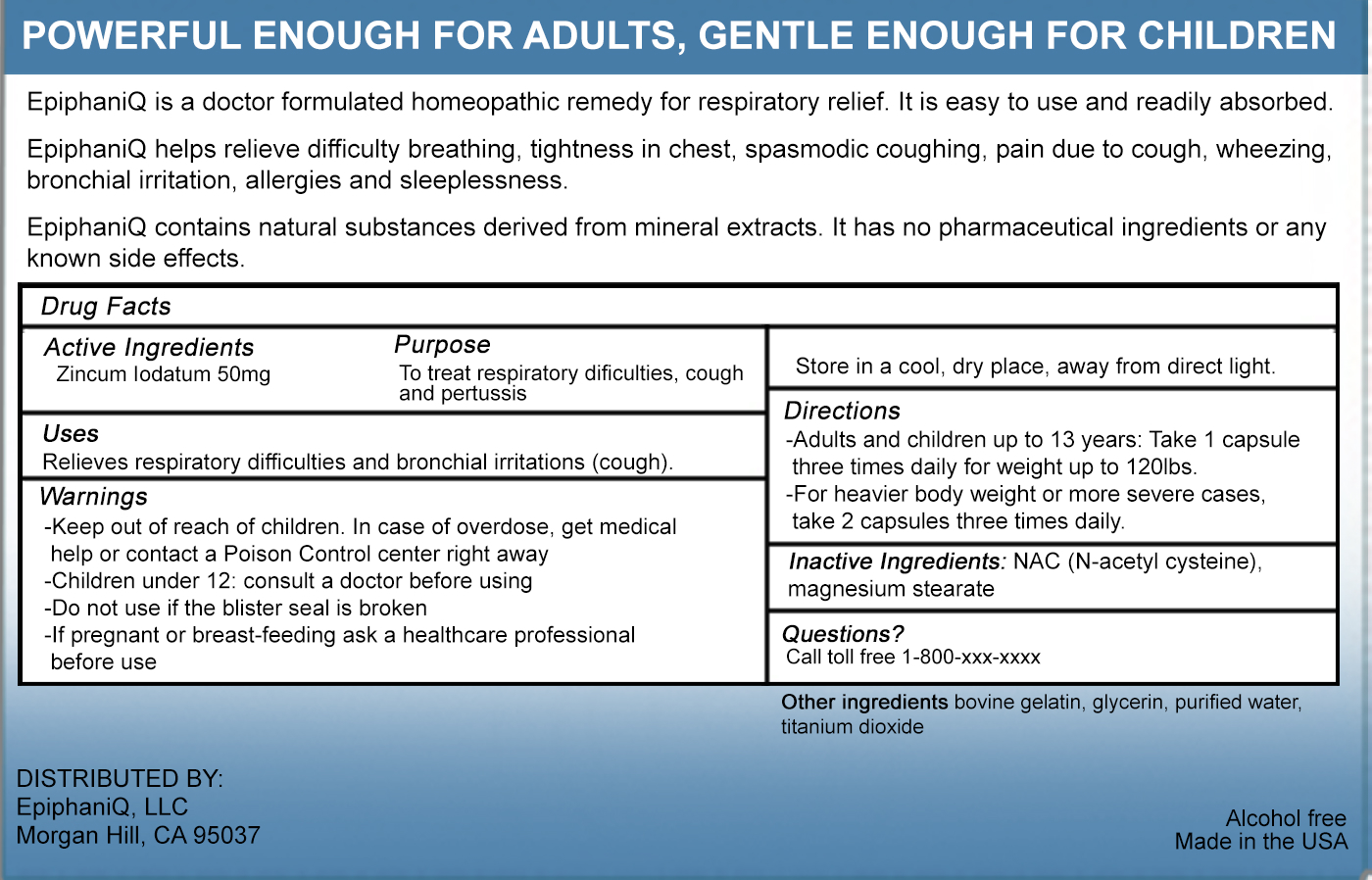 DRUG LABEL: EpiphaniQ
NDC: 79813-101 | Form: CAPSULE
Manufacturer: EpiphaniQ LLC
Category: homeopathic | Type: HUMAN OTC DRUG LABEL
Date: 20211229

ACTIVE INGREDIENTS: ZINC IODIDE 50 mg/1 1
INACTIVE INGREDIENTS: ACETYLCYSTEINE; MAGNESIUM STEARATE; GELATIN, UNSPECIFIED; GLYCERIN; WATER; TITANIUM DIOXIDE

EpiphaniQ 50mg/Capsule (79813-101)

ACTIVE INGREDIENT

ZINCUM IODATUM 50 MG

PURPOSE

TO TREAT RESPIRATORY DIFFICULTIES, COUGH AND PERTUSSIS

USES

Relieves respiratory difficulties and bronchial irritations (cough).

WARNINGS

- Children under 12: consult a doctor before using
- Do not use if the blister seal is broken
- If pregnant or breast-feeding ask a healthcare professional before use
- Store in a cool, dry place, away from direct light.

- Keep out of reach of children. In case of overdose, get medical help or contact a Poison Control center right away

DIRECTIONS

- Adults and children up to 13 years: Take 1 capsule three times daily for weight up to 120lbs.
- For heavier body weight or more severe cases, take 2 capsules three times

INACTIVE INGREDIENTS

NAC (N-acetyl cysteine), magnesium stearate

OTHER INGREDIENTS: BOVINE GELATIN, GLYCERIN, PURIFIED WATER, TITANIUM DIOXIDE

QUESTIONS

CALL TOLL FREE 1-800-XXX-XXXX